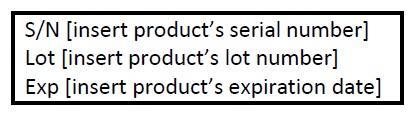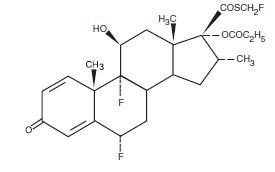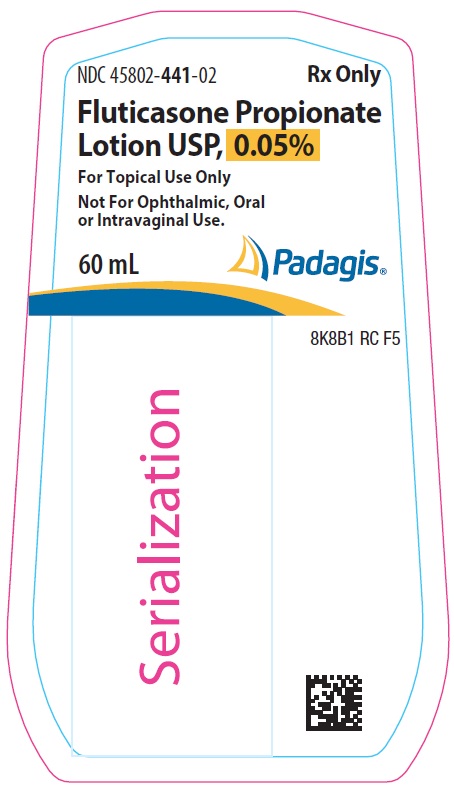 DRUG LABEL: fluticasone propionate
NDC: 45802-441 | Form: LOTION
Manufacturer: Padagis Israel Pharmaceuticals Ltd
Category: prescription | Type: HUMAN PRESCRIPTION DRUG LABEL
Date: 20240501

ACTIVE INGREDIENTS: FLUTICASONE PROPIONATE 0.5 mg/1 mL
INACTIVE INGREDIENTS: PROPYLENE GLYCOL; CETOSTEARYL ALCOHOL; ISOPROPYL MYRISTATE; MINERAL OIL; DIMETHICONE; CETETH-20; CITRIC ACID MONOHYDRATE; SODIUM CITRATE, UNSPECIFIED FORM; IMIDUREA; WATER; METHYLPARABEN; PROPYLPARABEN

HIGHLIGHTS OF PRESCRIBING INFORMATION

These highlights do not include all the information needed to use FLUTICASONE PROPIONATE LOTION safely and effectively. See full prescribing information for FLUTICASONE PROPIONATE LOTION.
FLUTICASONE PROPIONATE lotion, for topical use
Initial U.S. Approval: 1990

1 INDICATIONS AND USAGE

Fluticasone propionate lotion is a corticosteroid indicated for the relief of the inflammatory and pruritic manifestations of atopic dermatitis in patients 3 months of age and older. (1)

2 DOSAGE AND ADMINISTRATION

- Apply a thin film to the affected skin areas once daily. Rub in gently. (2)
- Discontinue use when control is achieved. (2)
- Reassess diagnosis if no improvement in 2 weeks. (2)
- The safety and efficacy of fluticasone propionate lotion have not been established beyond four weeks of use. (2)
- Avoid use under occlusion or application to diaper area. (2)
- Not for ophthalmic, oral, or intravaginal use. (2)

3 DOSAGE FORMS AND STRENGTHS

- Lotion, 0.05%, supplied in 60 mL bottles. (3)

4 CONTRAINDICATIONS

- None. (4)

5 WARNINGS AND PRECAUTIONS

- Hypothalamic-Pituitary-Adrenal (HPA) Axis Suppression: Reversible HPA axis suppression and resulting glucocorticoid insufficiency can occur during or after withdrawal of treatment. Risk factors include the use of high-potency topical corticosteroids, use over large surface area, prolonged use, use under occlusion, concomitant use with other corticosteroid-containing products, altered skin barrier, liver failure, and use in pediatric patients. Minimize risk by mitigating the risk factors and use product as recommended. Modify use if HPA axis suppression is suspected. (5.1, 8.4)
- Skin Irritation and Sensitization: fluticasone propionate lotion contains the excipient imidurea which releases formaldehyde as a breakdown product. Formaldehyde may cause allergic sensitization or irritation upon contact with the skin. Discontinue use if irritation or sensitization develops. (5.2)

6 ADVERSE REACTIONS

The most common adverse reactions (2%) were burning/stinging at the application site. (6.1)

To report SUSPECTED ADVERSE REACTIONS, contact Padagis® at 1-866-634-9120 or FDA at 1-800-FDA-1088 or www.fda.gov/medwatch.

FULL PRESCRIBING INFORMATION

1 INDICATIONS AND USAGE

Fluticasone propionate lotion is a corticosteroid indicated for the relief of the inflammatory and pruritic manifestations of atopic dermatitis in patients 3 months of age or older.

2 DOSAGE AND ADMINISTRATION

Apply a thin film of fluticasone propionate lotion to the affected skin areas once daily. Rub in gently.

Discontinue use when control is achieved. If no improvement is seen within 2 weeks, reassessment of the diagnosis may be necessary.

The safety and efficacy of fluticasone propionate lotion have not been established beyond 4 weeks of use.

Avoid use with occlusive dressings or application to the diaper area [see Warnings and Precautions (5.1) and (5.2)].

Fluticasone propionate lotion is for topical use only, and not for ophthalmic, oral, or intravaginal use.

3 DOSAGE FORMS AND STRENGTHS

Lotion, 0.05%. Each gram of fluticasone propionate lotion USP contains 0.5 mg fluticasone propionate USP in a white to off-white lotion base. Fluticasone propionate lotion USP is supplied in 60 mL bottles.

4 CONTRAINDICATIONS

None.

5 WARNINGS AND PRECAUTIONS

5.1 Hypothalamic-Pituitary-Adrenal (HPA) Axis Suppression and Other Adverse Endocrine Effects

Topical corticosteroids, including fluticasone propionate lotion can produce reversible HPA axis suppression with the potential for glucocorticoid insufficiency. Risk factors that predispose to HPA axis suppression include the use of high-potency topical corticosteroids, large treatment surface areas, prolonged use, use under occlusion, concomitant use of more than one corticosteroid-containing product, altered skin barrier, and liver failure. Pediatric patients may be at greater risk of HPA axis suppression due to their higher skin surface area to body mass ratios [see Use in Specific Populations (8.4)].

HPA axis suppression may occur during or after withdrawal of treatment. If HPA axis suppression is suspected, gradually withdraw the drug, reduce the frequency of application, or substitute a less potent topical corticosteroid. Evaluation of HPA axis suppression may be done by using the cosyntropin stimulation test.

The effects of fluticasone propionate lotion on HPA axis function in pediatric patients were investigated in two trials. Among a total of 89 evaluable subjects from the two trials who were treated with fluticasone propionate lotion twice daily for 3 to 4 weeks, a single subject with >90% body surface area treated showed laboratory evidence of transient suppression immediately post-treatment. The post cosyntropin stimulation test serum cortisol returned to a normal level (22.1 μg/dL) within one week of the final treatment visit [see Use In Specific Populations (8.4) and Clinical Pharmacology (12.2)].

Cushing’s syndrome, hyperglycemia, and unmasking of latent diabetes mellitus can also result from systemic absorption of topical corticosteroids.

Use of more than one corticosteroid-containing product at the same time may increase the total systemic absorption of topical corticosteroids.

5.2 Local Adverse Reactions

Fluticasone propionate lotion may cause local adverse reactions, including skin atrophy [see Adverse Reactions (6.1, 6.2)]. The risk is greater with use under occlusion and with higher potency products.

Fluticasone propionate lotion contains the excipient imidurea which releases formaldehyde as a breakdown product. Formaldehyde may cause allergic sensitization or irritation upon contact with the skin. Avoid using fluticasone propionate lotion in individuals with hypersensitivity to formaldehyde as it may prevent healing or worsen dermatitis.

If irritation develops, discontinue fluticasone propionate lotion and institute appropriate therapy.

Allergic Contact Dermatitis

Allergic contact dermatitis with corticosteroids is usually diagnosed by observing a failure to heal rather than noticing a clinical exacerbation. Such an observation can be corroborated with appropriate diagnostic patch testing. Discontinue fluticasone propionate lotion if appropriate.

5.3 Concomitant Skin Infections

If skin infections are present or develop at the treatment site, an appropriate antimicrobial agent should be used. If a favorable response does not occur promptly, discontinue use of fluticasone propionate lotion until the infection has been adequately controlled.

6 ADVERSE REACTIONS

The following adverse reactions are discussed in greater detail in other sections of the labeling:

- HPA Axis Suppression and Other Adverse Endocrine Effects [see Warnings and Precautions (5.1)]
- Local Adverse Reactions [see Warnings and Precautions (5.2)]
- Concomitant Skin Infections [see Warnings and Precautions (5.3)]

6.1 Clinical Trials Experience: Controlled Clinical Trials

Because clinical trials are conducted under widely varying conditions, adverse reaction rates observed in the clinical trials of a drug cannot be directly compared to rates in the clinical trials of another drug and may not reflect the rates observed in practice.

In 2 multicenter vehicle-controlled clinical trials of once-daily application of fluticasone propionate lotion by 196 adult and 242 pediatric patients, the total incidence of adverse reactions considered drug related by investigators was approximately 4%. These were local cutaneous reactions, usually mild and self-limiting, and consisted primarily of burning/stinging (2%). All other drug-related events occurred with an incidence of less than 1%, and included were contact dermatitis, exacerbation of atopic dermatitis, folliculitis of legs, pruritus, pustules on arm, rash, and skin infection. See Table 1.

The incidence of adverse reactions between the 242 pediatric subjects (age 3 months to < 17 years) and 196 adult subjects (17 years or older) was similar (4% and 5%, respectively).

Table 1: Adverse Reactions from Controlled Clinical Trials (N=438)

Adverse Reactions | Fluticasone propionate lotion n=221 | Vehicle n=217
Burning/Stinging skin | 4 (2%) | 3 (1%)
Contact Dermatitis | 0 | 1 (<1%)
Exacerbation of Atopic dermatitis | 0 | 1 (<1%)
Folliculitis of legs | 2 (<1%) | 0
Irritant Contact Dermatitis | 0 | 1 (<1%)
Pruritus | 1 (<1%) | 1 (<1%)
Pustules on Arms | 1 (<1%) | 0
Rash | 1 (<1%) | 2 (<1%)
Skin Infection | 0 | 3 (1%)

During the clinical trials, eczema herpeticum occurred in a 33-year old male patient treated with fluticasone propionate lotion.

Table 2 summarizes all adverse events by body system that occurred in at least 1% of patients in either the drug or vehicle group in the phase 3 controlled clinical trials.

Table 2: Adverse Events Occurring in ≥1% of Patients from Either Arm from Controlled Clinical Trials (n=438)

Body System | Fluticasone propionate lotion (N=221) | Vehicle Lotion (N=217)
Any Adverse Event | 77 (35%) | 82 (38%)
Skin
Burning and Stinging | 4 (2%) | 3 (1%)
Pruritus | 3 (1%) | 5 (2%)
Rash | 2 (<1%) | 3 (1%)
Skin Infection | 0 | 3 (1%)
Ear, Nose, Throat
Common Cold | 9 (4%) | 5 (2%)
Ear Infection | 3 (1%) | 3 (1%)
Nasal Sinus Infection | 2 (<1%) | 4 (2%)
Rhinitis | 1 (<1%) | 3 (1%)
Upper Respiratory Tract Infection | 6 (3%) | 7 (3%)
Gastrointestinal
Normal Tooth Eruption | 2 (<1%) | 3 (1%)
Diarrhea | 3 (1%) | 0
Vomiting | 3 (1%) | 2 (<1%)
Lower Respiratory
Cough | 7 (3%) | 6 (3%)
Influenza | 5 (2%) | 0
Wheeze | 0 | 3 (1%)
Neurology
Headache | 4 (2%) | 5 (2%)
Non-Site Specific
Fever | 8 (4%) | 8 (4%)
Seasonal Allergy | 2 (<1%) | 3 (1%)

6.2 Clinical Trials Experience: Pediatric Open Label Trials

In an open label HPA axis suppression trial of 44 pediatric subjects (ages ≥3 months to ≤6 years) fluticasone propionate lotion was applied twice daily (rather than the indicated dosing regimen of once daily) to at least 35% of body surface area for 3 or 4 weeks. Subjects whose lesions cleared after 2 or 3 weeks of treatment continued to apply fluticasone propionate lotion for an additional week. The overall incidence of adverse reactions was 14%. These were local, cutaneous reactions and included dry skin (7%), stinging at application site (5%), and excoriation (2%). Additionally, a 4-month-old patient treated with fluticasone propionate lotion had marked elevations of the hepatic enzymes AST and ALT. [see Use in Specific Populations (8.4)]

In another open label HPA axis suppression trial in which fluticasone propionate lotion was also applied twice daily (rather than the indicated dosing regimen of once daily), 56 pediatric subjects (ages ≥3 months to 12 months), were enrolled [see Use in Specific Populations (8.4)].

The adverse reactions included 2 cases of Herpes simplex at the application site (3.6%) and 3 cases of bacterial skin infections (5.4%).

6.3 Postmarketing Experience

The following local adverse reactions have been identified during post-approval use of fluticasone propionate lotion: erythema, edema/swelling, and bleeding.

The following systemic adverse reactions have been identified during post-approval use of fluticasone propionate cream and fluticasone propionate ointment: immunosuppression/Pneumocystis jirovecii pneumonia/leukopenia/thrombocytopenia; hyperglycemia/ glycosuria; Cushing syndrome; generalized body edema/blurred vision; and acute urticarial reaction (edema, urticaria, pruritus, and throat swelling).

The following local adverse reactions have also been reported with the use of topical corticosteroids, and they may occur more frequently with the use of occlusive dressings or higher potency corticosteroids. These reactions include: acneiform eruptions, hypopigmentation, perioral dermatitis, skin atrophy, striae, hypertrichosis and miliaria.

Because these reactions are reported voluntarily from a population of uncertain size, it is not always possible to reliably estimate their frequency or establish a causal relationship to drug exposure.

8 USE IN SPECIFIC POPULATIONS

8.1 Pregnancy

Pregnancy Category C

There are no adequate and well-controlled studies in pregnant women. Therefore, fluticasone propionate lotion should be used during pregnancy only if the potential benefit justifies the potential risk to the fetus.

Systemic embryofetal development studies were conducted in mice, rats and rabbits.

Subcutaneous doses of 15, 45 and 150 μg/kg/day of fluticasone propionate were administered to pregnant female mice from gestation days 6 to 15. A teratogenic effect characteristic of corticosteroids (cleft palate) was noted after administration of 45 and 150 μg/kg/day (less than the MRHD in adults based on body surface area comparisons) in this study. No treatment related effects on embryofetal toxicity or teratogenicity were noted at 15 μg/kg/day (less than the MRHD in adults based on body surface area comparisons).

Subcutaneous doses of 10, 30 and 100 μg/kg/day of fluticasone propionate were administered to pregnant female rats in two embryofetal development studies (one study administered fluticasone propionate from gestation days 6 to 15 and the other study from gestation days 7 to 17). In the presence of maternal toxicity, fetal effects noted at 100 μg/kg/day (less than the MRHD in adults based on body surface area comparisons) included decreased fetal weights, omphalocele, cleft palate, and retarded skeletal ossification. No treatment related effects on embryofetal toxicity or teratogenicity were noted at 10 μg/kg/day (less than the MRHD in adults based on body surface area comparisons).

Subcutaneous doses of 0.08, 0.57 and 4 μg/kg/day of fluticasone propionate were administered to pregnant female rabbits from gestation days 6 to 18. Fetal effects noted at 4 μg/kg/day (less than the MRHD in adults based on body surface area comparisons) included decreased fetal weights, cleft palate and retarded skeletal ossification. No treatment related effects on embryofetal toxicity or teratogenicity were noted at 0.57 μg/kg/day (less than the MRHD in adults based on body surface area comparisons).

Oral doses of 3, 30 and 300 μg/kg/day fluticasone propionate were administered to pregnant female rabbits from gestation days 8 to 20. No fetal or teratogenic effects were noted at oral doses up to 300 μg/kg/day (less than the MRHD in adults based on body surface area comparisons) in this study. However, no fluticasone propionate was detected in the plasma in this study, consistent with the established low bioavailability following oral administration.

Fluticasone propionate crossed the placenta following administration of a subcutaneous or an oral dose of 100 μg/kg tritiated fluticasone propionate to pregnant rats.

8.3 Nursing Mothers

Systemically administered corticosteroids appear in human milk and can suppress growth, interfere with endogenous corticosteroid production, or cause other untoward effects. It is not known whether topical administration of corticosteroids could result in sufficient systemic absorption to produce detectable quantities in human milk. Because many drugs are excreted in human milk, caution should be exercised when fluticasone propionate lotion is administered to a nursing woman.

8.4 Pediatric Use

Fluticasone propionate lotion may be used in pediatric patients as young as 3 months of age. The safety and effectiveness of fluticasone propionate lotion in pediatric patients below 3 months of age have not been established.

Because of a higher ratio of skin surface area to body mass, pediatric patients are at a greater risk than adults of systemic effects when treated with topical drugs. They are, therefore, also at greater risk of HPA axis suppression and adrenal insufficiency upon the use of topical corticosteroids [see Warnings and Precautions (5.1)].

In an HPA axis suppression trial, none of the 40 evaluable pediatric subjects, 4 months old to < 6 years old, with moderate to severe atopic dermatitis covering ≥ 35% Body Surface Area (BSA) who were treated with an exaggerated dosing regimen (twice daily) of fluticasone propionate lotion experienced adrenal suppression (defined as a 30-minute post-stimulation cortisol level ≤18 micrograms/dL) [see Warnings and Precautions (5.1) and Clinical Pharmacology (12.2)].

In another HPA axis suppression trial, one of 49 (2%) evaluable pediatric subjects, 3 months to 11 months old, with moderate to severe atopic dermatitis covering ≥ 35% Body Surface Area (BSA) who applied an exaggerated dosing regimen (twice daily) of fluticasone propionate lotion experienced reversible adrenal suppression (defined as a 30-minute post-stimulation cortisol level ≤18 micrograms/dL) following 4 weeks of therapy [see Warnings and Precautions (5.1) and Clinical Pharmacology (12.2)].

Systemic effects such as Cushing's syndrome, linear growth retardation, delayed weight gain, and intracranial hypertension have been reported in pediatric patients, especially those with prolonged exposure to large doses of high-potency topical corticosteroids, or concomitant use of more than one corticosteroid product.

Local adverse reactions including skin atrophy have also been reported with use of topical corticosteroids in pediatric patients.

Parents of pediatric patients should be advised not to use this medication in the treatment of diaper dermatitis unless directed by a physician. Fluticasone propionate lotion should not be applied in the diaper areas as diapers or plastic pants may constitute occlusive dressing.

8.5 Geriatric Use

A limited number of patients above 65 years of age have been treated with fluticasone propionate lotion in US and non-US clinical trials. Specifically only 8 patients above 65 years of age were treated with fluticasone propionate lotion in controlled clinical trials. The number of patients is too small to permit separate analyses of efficacy and safety.

11 DESCRIPTION

Fluticasone propionate lotion USP, 0.05% contains fluticasone propionate [S-Fluoromethyl 6α, 9α-difluoro-11β-hydroxy-16α-methyl-3-oxo-17α-propionyloxyandrosta-1,4-diene-17β-carbothioate], a synthetic fluorinated corticosteroid, for topical use. The topical corticosteroids constitute a class of primarily synthetic steroids used as anti-inflammatory and antipruritic agents.

Chemically, fluticasone propionate, USP is C25H31F3O5S. It has the following structural formula:

Fluticasone propionate USP has a molecular weight of 500.6. It is a white to off-white powder and is practically insoluble in water, freely soluble in dimethyl sulfoxide and dimethylformamide, and slightly soluble in methanol and 95% ethanol.

Each gram of fluticasone propionate lotion USP contains 0.5 mg fluticasone propionate USP in a white to off white lotion base of anhydrous citric acid, cetomacrogol 1000, cetostearyl alcohol, dimethicone 360, imidurea, isopropyl myristate, methylparaben, mineral oil, propylene glycol, propylparaben, purified water, and sodium citrate.

12 CLINICAL PHARMACOLOGY

12.1 Mechanism of Action

Corticosteroids play a role in cellular signaling, immune function, inflammation, and protein regulation; however, the precise mechanism of action of fluticasone propionate lotion in atopic dermatitis is unknown.

12.2 Pharmacodynamics

Vasoconstrictor Assay

Trials performed with fluticasone propionate lotion indicate that it is in the medium range of potency as demonstrated in vasoconstrictor trials in healthy subjects when compared with other topical corticosteroids. However, similar blanching scores do not necessarily imply therapeutic equivalence.

Hypothalamic-Pituitary-Adrenal (HPA) Axis Suppression

In an open label HPA axis suppression trial (Trial A), 42 pediatric subjects (ages 4 months to <6 years) with moderate to severe atopic dermatitis covering ≥ 35% Body Surface Area (BSA) who were treated with an exaggerated dosing regimen of fluticasone propionate lotion twice daily (rather than the indicated dosing regimen of once daily) for at least 3 to 4 weeks were assessed for HPA axis suppression. The mean BSA treated was 65%. None of the 40 evaluable subjects were suppressed. The criterion for HPA axis suppression was a serum cortisol level of less than or equal to 18 micrograms per deciliter at 30-minutes after cosyntropin stimulation.

Another open label HPA axis suppression trial (Trial B) enrolled 56 pediatric subjects (ages 3 months to 11 months) with moderate to severe atopic dermatitis covering ≥ 35% BSA. Subjects were treated with an exaggerated dosing regimen of fluticasone propionate lotion twice daily over a period of 3 or 4 weeks. The mean BSA treated was 54%. Out of 56 subjects, 49 were considered evaluable with respect to their adrenal axis function post-treatment. One of 49 subjects showed laboratory evidence of suppression immediately post treatment. The criterion for HPA axis suppression was a serum cortisol level of less than or equal to 18 micrograms per deciliter at 30-minutes after cosyntropin stimulation. Repeated test one week later showed the post cosyntropin stimulation testing serum cortisol returned to normal level (22.1 μg/dL). This 4-month old subject had a baseline treatment BSA of 94% and was reported to have received 100% of the twice-daily applications of fluticasone propionate lotion, 0.05% over the 27 day treatment period.

12.3 Pharmacokinetics

Absorption

The extent of percutaneous absorption of topical corticosteroids is determined by many factors, including the vehicle and the integrity of the epidermal barrier. Occlusive dressing enhances penetration. Topical corticosteroids can be absorbed from normal intact skin. Inflammation and/or other disease processes in the skin increase percutaneous absorption.

Plasma fluticasone levels were measured in a subset of subjects 2 to 5 years and 11 months of age in HPA axis suppression trial (Trial A) described above. A total of 13 (62%) of 21 subjects tested had measurable fluticasone at the end of 3 to 4 weeks of treatment. The mean ± SD fluticasone plasma concentration was 0.16 ± 0.23 ng/mL. Three subjects aged 3, 4, and 4 years had fluticasone concentrations over 0.30 ng/mL, with one of them having a concentration of 0.82 ng/mL. No data were obtained for subjects < 2 years of age.

Distribution

The percentage of fluticasone propionate bound to human plasma proteins averaged 91%. Fluticasone propionate is weakly and reversibly bound to erythrocytes. Fluticasone propionate is not significantly bound to human transcortin.

Metabolism

No metabolites of fluticasone propionate were detected in an in vitro study of radiolabeled fluticasone propionate incubated in a human skin homogenate.

Fluticasone propionate is metabolized in the liver by cytochrome P450 3A4-mediated hydrolysis of the 5-fluoromethyl carbothiolate grouping. This transformation occurs in 1 metabolic step to produce the inactive 17β-carboxylic acid metabolite, the only known metabolite detected in man. This metabolite has approximately 2000 times less affinity than the parent drug for the glucocorticoid receptor of human lung cytosol in vitro and negligible pharmacological activity in animal studies. Other metabolites detected in vitro using cultured human hepatoma cells have not been detected in man.

13 NONCLINICAL TOXICOLOGY

13.1 Carcinogenesis, Mutagenesis, Impairment of Fertility

In an oral (gavage) mouse carcinogenicity study, doses of 0.1, 0.3 and 1 mg/kg/day fluticasone propionate were administered to mice for 18 months. Fluticasone propionate demonstrated no tumorigenic potential at oral doses up to 1 mg/kg/day (less than the MRHD in adults based on body surface area comparisons) in this study.

In a dermal mouse carcinogenicity study, 0.05% fluticasone propionate ointment (40 μl) was topically administered for 1, 3 or 7 days/week for 80 weeks. Fluticasone propionate demonstrated no tumorigenic potential at dermal doses up to 6.7 μg/kg/day (less than the MRHD in adults based on body surface area comparisons) in this study.

Fluticasone propionate revealed no evidence of mutagenic or clastogenic potential based on the results of five in vitro genotoxicity tests (Ames assay, E. coli fluctuation test, S. cerevisiae gene conversion test, Chinese hamster ovary cell chromosome aberration assay and human lymphocyte chromosome aberration assay) and one in vivo genotoxicity test (mouse micronucleus assay).

No evidence of impairment of fertility or effect on mating performance was observed in a fertility and general reproductive performance study conducted in male and female rats at subcutaneous doses up to 50 μg/kg/day (less than the MRHD in adults based on body surface area comparisons).

14 CLINICAL STUDIES

Fluticasone propionate lotion applied once daily was superior to vehicle in the treatment of atopic dermatitis in two clinical trials. The two trials enrolled 438 subjects with atopic dermatitis aged 3 months and older, of which 169 subjects were selected as having clinically significant signs of erythema, infiltration/papulation, and erosion/oozing/crusting at baseline. Clinically significant was defined as having moderate or severe involvement for at least two of the three signs (erythema, infiltrations/papulation, or erosion/oozing/crusting), in at least 2 body regions. Subjects who had moderate to severe disease in a single body region were excluded from the analysis.

Table 3 presents the percentage of subjects who completely cleared of erythema, infiltration/papulation and erosion/oozing/crusting at Week 4 out of those subjects with clinically significant baseline signs.

Table 3: Complete Clearance Rate For Patients with Clinically Significant Signs at Baseline

 | Fluticasone propionate lotion | Vehicle
Study 1 | 9/45 (20%) | 0/37 (0%)
Study 2 | 7/44 (16%) | 1/43 (2%)

16 HOW SUPPLIED/STORAGE AND HANDLING

Fluticasone Propionate Lotion USP, 0.05% is white to off-white in color, and supplied as follows:

60 mL bottle NDC 45802-441-02

Store at 20-25°C (68-77°F) [see USP Controlled Room Temperature].

Do not refrigerate, and keep container tightly closed.

17 PATIENT COUNSELING INFORMATION

Advise the patient to read the FDA-approved patient labeling (Patient Information).

Administration Instructions

Advise the patient of appropriate fluticasone propionate lotion administration instructions, including those that will mitigate HPA-Axis suppression [see Warnings and Precautions (5.1)] and local adverse reactions [see Warnings and Precautions (5.2)]:

- Discontinue therapy when control is achieved in less than 4 weeks; if no improvement is seen within 2 weeks, contact the healthcare provider.
- Avoid contact with the eyes.
- Do not bandage the treated skin area, or cover or wrap it to cause occlusion unless directed by the healthcare provider.
- Do not use fluticasone propionate lotion in the treatment of diaper dermatitis unless directed by the healthcare provider, as diapers or plastic pants may constitute occlusive dressing and enhance absorption.
- Do not use on the face, underarms, or groin areas unless directed by the healthcare provider.

Local Adverse Reactions

Advise the patient to report any signs of local adverse reactions to their healthcare provider [see Warnings and Precautions (5.2)].

- Advise patients to report to their healthcare provider if they are allergic to formaldehyde.

Manufactured by Padagis®

Yeruham, Israel

www.padagis.com

Rev 05-24

8K800 RC PH6

PATIENT INFORMATION

Fluticasone Propionate (floo-TIK-a-sone PROE-pee-oh-nate)Lotion USP, 0.05%

Important: Fluticasone propionate lotion is for use on skin only (topical). Do not get fluticasone propionate lotion near or in your eyes, mouth, or vagina.

Read this Patient Information before you start using fluticasone propionate lotion and each time you get a refill. There may be new information. This information does not take the place of talking to your healthcare provider about your medical condition or treatment.

What is fluticasone propionate lotion?

Fluticasone propionate lotion is a prescription corticosteroid medicine used on the skin (topical) for the relief of inflammation and itching caused by certain skin conditions, including atopic dermatitis and eczema in people 3 months of age and older.

It is not known if fluticasone propionate lotion is safe and effective in children under 3 months of age.

Before using fluticasone propionate lotion, tell your healthcare provider about all of your medical conditions, including if you:

- have a skin infection at the site to be treated. You may also need medicine to treat the skin infection.
- have adrenal gland problems
- have liver problems
- have diabetes
- have thinning skin (atrophy) at the site to be treated
- are allergic to formaldehyde. If you are allergic to formaldehyde, fluticasone propionate lotion may cause skin irritation, prevent your skin from healing or worsen your skin condition.
- are pregnant or plan to become pregnant. It is not known if fluticasone propionate lotion will harm your unborn baby.
- are breastfeeding or plan to breastfeed. It is not known if fluticasone propionate can pass into your breast milk and harm your baby.

Tell your healthcare provider about all the medicines you take, including prescription and over-the-counter medicines, vitamins, and herbal supplements. Especially tell your healthcare provider if you take other corticosteroid medicines by mouth or use other products on your skin that contain corticosteroids.

How should I use fluticasone propionate lotion?

- Use fluticasone propionate lotion exactly as your healthcare provider tells you to use it.
- Apply a thin film of fluticasone propionate lotion to the affected area 1 time each day. Gently rub into your skin.
- Do not bandage, cover, or wrap the treated area unless your healthcare provider tells you to. Do not apply fluticasone propionate lotion to dermatitis in the diaper area unless your healthcare provider tells you to.
- Wash your hands after applying fluticasone propionate lotion, unless your hands are being treated.
- Tell your healthcare provider if your symptoms get worse with fluticasone propionate lotion or if your symptoms do not improve after 2 weeks of treatment. It is not known if fluticasone propionate lotion is safe or effective when used more than 4 weeks.

What are possible side effects with fluticasone propionate lotion?

Fluticasone propionate lotion may cause serious side effects, including:

- Fluticasone propionate lotion can pass through your skin and may cause adrenal gland problems. This is more likely to happen if you use fluticasone propionate lotion for too long, use it over a large treatment area, use it with other topical medicines that contain corticosteroids, cover the treated area, or have liver failure. Your healthcare provider may do blood tests to check your adrenal gland function during and after treatment with fluticasone propionate lotion.
- Skin problems, including skin reactions or thinning of your skin (atrophy), skin infections, and allergic reactions (allergic contact dermatitis) at the treatment site. Tell your healthcare provider if you get any skin reactions such as pain, tenderness, swelling, or healing problems.

The most common side effects of fluticasone propionate lotion include burning and stinging at the treatment site.

These are not all the possible side effects with fluticasone propionate lotion. Call your doctor for medical advice about side effects. You may report side effects to FDA at 1-800-FDA-1088.

How should I store fluticasone propionate lotion?

- Store fluticasone propionate lotion at 20-25°C (68-77°F) [see USP Controlled Room Temperature].
- Do not refrigerate.
- Keep the bottle tightly closed.

Keep fluticasone propionate lotion and all medicines out of the reach of children.

General information about the safe and effective use of fluticasone propionate lotion.

Medicines are sometimes prescribed for purposes other than those listed in a Patient Information leaflet. Do not use fluticasone propionate lotion for a condition for which it was not prescribed. Do not give fluticasone propionate lotion to other people, even if they have the same symptoms you have. It may harm them. You can ask your pharmacist or healthcare provider for information about fluticasone propionate lotion that is written for health professionals.

What are the ingredients in fluticasone propionate lotion?

Active ingredient: fluticasone propionate

Inactive ingredients: anhydrous citric acid, cetomacrogol 1000, cetostearyl alcohol, dimethicone 360, imidurea, isopropyl myristate, methylparaben, mineral oil, propylene glycol, propylparaben, purified water, and sodium citrate.

For more information, go to www.padagis.com or call 1-866-634-9120.

This Patient Information has been approved by the U.S. Food and Drug Administration.

Manufactured by Padagis®

Yeruham, Israel

www.padagis.com

Rev 05-24

8K800 RC PH6

PACKAGE/LABEL PRINCIPAL DISPLAY PANEL

NDC 45802-441-02

Rx Only

Fluticasone Propionate Lotion USP, 0.05%

For Topical Use Only

Not For Ophthalmic, Oral or Intravaginal Use.

60 mL

The following image is a placeholder representing the product identifier that is either affixed or imprinted on the drug package label during the packaging operation.